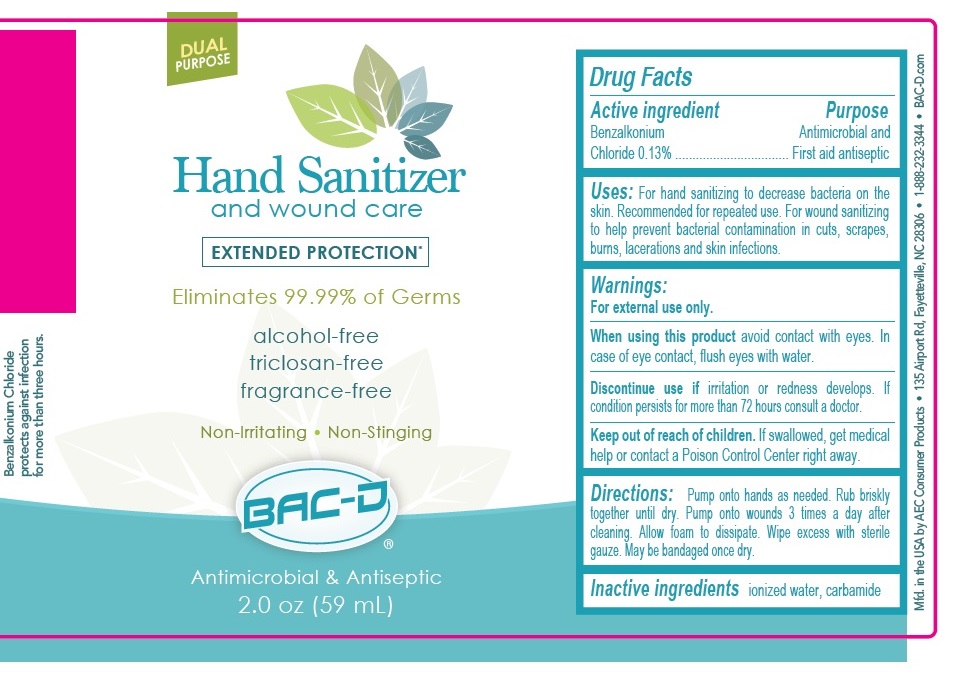 DRUG LABEL: BAC-D
NDC: 86089-400 | Form: SPRAY
Manufacturer: AEC CONSUMER PRODUCTS
Category: otc | Type: HUMAN OTC DRUG LABEL
Date: 20220103

ACTIVE INGREDIENTS: BENZALKONIUM CHLORIDE 0.13 g/100 mL
INACTIVE INGREDIENTS: WATER; UREA

BAC-D Hand and Wound Sanitizer

Active ingredient

Benzalkonium Chloride 0.13%

Purpose

Antimicrobial and First aid antiseptic

Uses:

•For hand sanitizing to decrease bacteria on the skin. Recommended for repeated use. •For wound sanitizing to help prevent bacterial contamination in cuts, scrapes, burns, lacerations and skin infections.

Warnings:

For external use only. Avoid contact with eyes. In case of eye contact, flush eyes with water. Discontinue use if irritation or redness develops. If condition persists for more than 72 hours consult a doctor.

Keep out of reach of children. If swallowed, get medical help or contact a Poison Control Center right away.

Directions:

•Spray hands as needed. •Spray wounds 3 times a day after cleaning.

Inactive ingredients:

ionized water, carbamide

DUAL PURPOSE

EXTENDED PROTECTION*

Eliminates 99.99% of Germs

alcohol-free | triclosan-free

Non-Irritating • Non-Stinging

Antibacterial & Antiseptic

MADE IN THE U.S.A.

Manufactured for

AEC Consumer Products

4525 Campground Road

Fayetteville, NC 28314

www.BAC-D.com

910-987-7964

*Studies show Benzalkonium Chloride protects against infection for more than three hours.